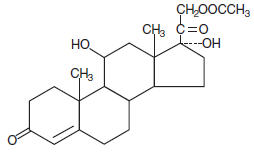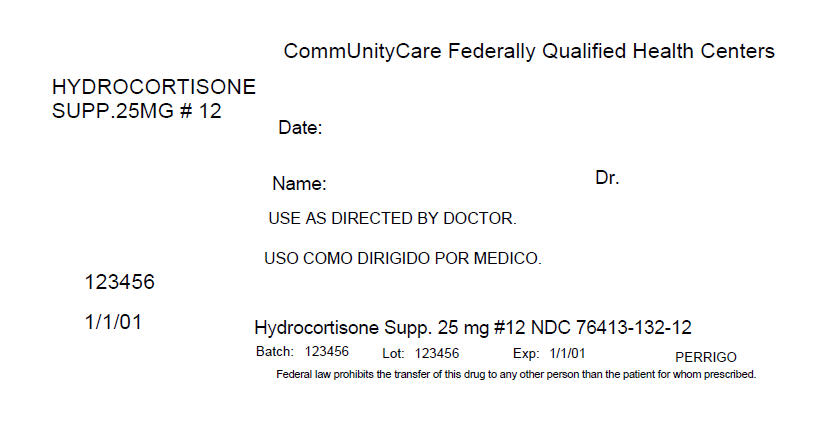 DRUG LABEL: Hydrocortisone Acetate
NDC: 76413-132 | Form: SUPPOSITORY
Manufacturer: Central Texas Community Health Centers
Category: prescription | Type: HUMAN PRESCRIPTION DRUG LABEL
Date: 20160408

ACTIVE INGREDIENTS: HYDROCORTISONE ACETATE 25 mg/1 1

Hydrocortisone Acetate
Suppositories 25 mg

DESCRIPTION

Each suppository for rectal administration contains 25 mg hydrocortisone acetate USP in a hydrogenated cocoglyceride base. Hydrocortisone acetate is a corticosteroid.

Chemically, hydrocortisone acetate is pregn-4-ene-3, 20 dione, 21- (acetyloxy)-11, 17-dihydroxy-, (11β)- with the following structural formula:

CLINICAL PHARMACOLOGY

In normal subjects, about 26 percent of hydrocortisone acetate is absorbed when the hydrocortisone acetate suppository is applied to the rectum. Absorption of hydrocortisone acetate may vary across abraded or inflamed surfaces.

Topical steroids are primarily effective because of their anti-inflammatory, antipruritic and vasoconstrictive action.

INDICATIONS AND USAGE

For use in inflamed hemorrhoids, post irradiation (factitial) proctitis, as an adjunct in the treatment of chronic ulcerative colitis, cryptitis, other inflammatory conditions of the anorectum, and pruritus ani.

CONTRAINDICATIONS

Hydrocortisone acetate suppositories are contraindicated in those patients with a history of hypersensitivity to any of the components.

PRECAUTIONS

Do not use unless adequate proctologic examination is made.

If irritation develops, the product should be discontinued and appropriate therapy instituted.

In the presence of an infection, the use of an appropriate antifungal or antibacterial agent should be instituted. If a favorable response does not occur promptly, the corticosteroid should be discontinued until the infection has been adequately controlled.

No long-term studies in animals have been performed to evaluate the carcinogenic potential of corticosteroid suppositories.

PREGNANCY CATEGORY C

In laboratory animals, topical steroids have been associated with an increase in the incidence of fetal abnormalities when gestating females have been exposed to rather low dosage levels. There are no adequate and well-controlled studies in pregnant women.

It is not known whether this drug is excreted in human milk.

Until adequate studies in pregnant or lactating women have been conducted, this drug should be used during pregnancy or by nursing mothers only when clearly needed and when the potential benefits outweigh the potential risks.

ADVERSE REACTIONS

The following local adverse reactions have been reported with corticosteroid suppositories:

1. Burning
2. Itching
3. Irritation
4. Dryness

5. Folliculitis
6. Hypopigmentation
7. Allergic Contact Dermatitis
8. Secondary Infection

Drug abuse and dependence have not been reported in patients treated with hydrocortisone acetate suppositories.

OVERDOSAGE

If signs and symptoms of systemic overdosage occur, discontinue use.

DOSAGE AND ADMINISTRATION

Usual dosage:

One suppository in the rectum morning and night for two weeks, in nonspecific proctitis. In more severe cases, one suppository three times daily; or two suppositories twice daily. In factitial proctitis, recommended therapy is six to eight weeks or less, according to response.

HOW SUPPLIED

Hydrocortisone acetate suppositories are easy to open, color coded and available in cartons of:

12's | NDC 76413-132-12

STORAGE AND HANDLING

Store at controlled room temperature 15° to 30°C (59° to 86°F). Protect from freezing.

Manufactured By
Perrigo®
Minneapolis, MN 55427
(01-12)

PRINCIPAL DISPLAY PANEL - 12 Packet Box Label

CommUnityCare Federally Qualified Health Centers

HYDROCORTISONE
SUPP.25MG # 12

Date:

Name:
Dr.

USE AS DIRECTED BY DOCTOR.

123456

1/1/01

Hydrocortisone Supp. 25 mg #12 NDC 76413-132-12

Batch: 123456
Lot: 123456
Exp: 1/1/01
PERRIGO

Federal law prohibits the transfer of this drug to any other person than the patient for whom prescribed.